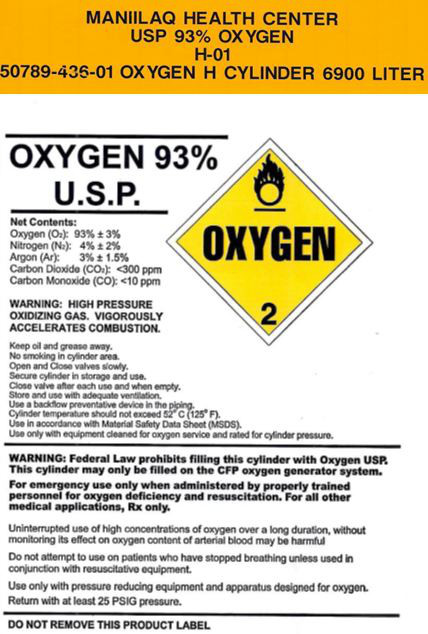 DRUG LABEL: Oxygen 
NDC: 50789-436 | Form: GAS
Manufacturer: Maniilaq Association
Category: prescription | Type: HUMAN PRESCRIPTION DRUG LABEL
Date: 20120606

ACTIVE INGREDIENTS: Oxygen 930 mL/1 L
INACTIVE INGREDIENTS: Nitrogen; Argon; Carbon Dioxide; Carbon Monoxide

PRINCIPAL DISPLAY PANEL

MANIILAQ HEALTH CENTER
USP 93% OXYGEN
H-01
50789-436-01 OXYGEN H CYLINDER 6900 LITER

OXYGEN 93%
U.S.P.

OXYGEN
2

Net Contents:
Oxygen (O2): 93% ± 3%
Nitrogen (N2): 4% ± 2%
Argon (Ar): 3% ± 1.5%
Carbon Dioxide (CO2): <300 ppm
Carbon Monoxide (CO): <10 ppm

WARNING: HIGH PRESSURE
OXIDIZING GAS. VIGOROUSLY
ACCELERATES COMBUSTION.

Keep oil and grease away.
No smoking in cylinder area.
Open and Close valves slowly.
Secure cylinder in storage and use.
Close valve after each use and when empty.
Store and use with adequate ventalation.
Use a backflow preventative device in the piping.
Cylinder temperature should not exceed 52° C (125° F).
Use in accordance with Material Safety Data Sheet (MSDS).
Use only with equipment cleaned for oxygen service and rated for cylinder pressure.

WARNING: Federal Law prohibits filling this cylinder with Oxygen USP.
This cylinder may only be filled on the CFP oxygen generator system.

For emergency use only when administered by properly trained
personnel for oxygen deficiency and resuscitation. For all other
medical applications, Rx only.

Uniterrupted use of high concentrations of oxygen over a long duration, without
monitoring its effect on oxygen content of arterial blood may be harmful

Do not attempt to use on patients who have stopped breathing unless used in
conjunction with resuscitative equipment.

Use only with pressure reducing equipment and apparatus designed for oxygen.
Return with at least 25 PSIG pressure.

DO NOT REMOVE THIS PRODUCT LABEL